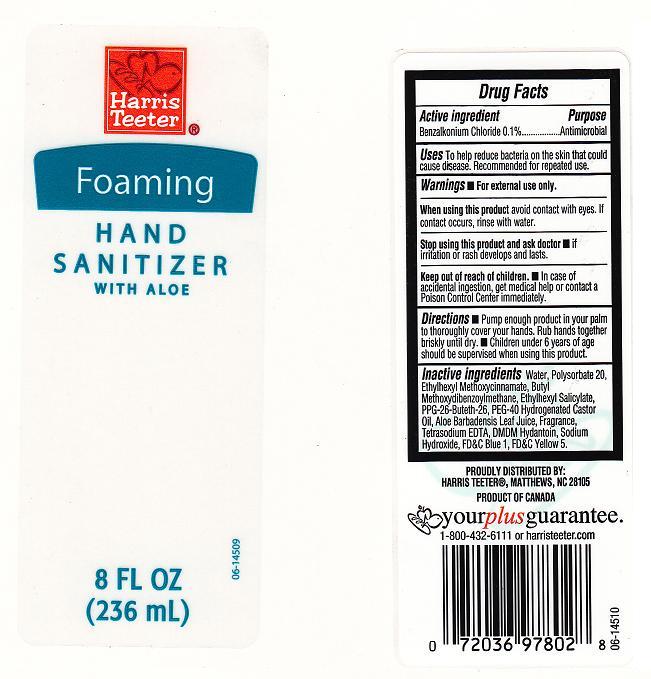 DRUG LABEL: FOAMING HAND SANITIZER
NDC: 72036-240 | Form: LIQUID
Manufacturer: HARRIS TEETER
Category: otc | Type: HUMAN OTC DRUG LABEL
Date: 20101116

ACTIVE INGREDIENTS: BENZALKONIUM CHLORIDE 0.1000 mL/100 mL
INACTIVE INGREDIENTS: WATER; POLYSORBATE 20; OCTINOXATE; AVOBENZONE; OCTISALATE; PROPYLENE OXIDE; POLYOXYL 40 HYDROGENATED CASTOR OIL; ALOE VERA LEAF; EDETATE SODIUM; DMDM HYDANTOIN; CITRIC ACID MONOHYDRATE; FD&C BLUE NO. 1; FD&C YELLOW NO. 5

DRUG FACTS BOX (BACK LABEL)

ACTIVE INGREDIENT

BENZALKONIUM CHLORIDE 0.1%

Purpose

Antimicrobial

Uses

To help reduce bacteria on the skin that could cause disease. Recommended for repeated use.

Warnings

For external use only.

When using this product

avoid contact with eyes. If contact occurs, rinse with water.

Stop using and ask a doctor

if irritation or rash develops and lasts

Keep out of reach of children

In case of accidental ingestion, get medical help or contact a Poison Control Center immediately.

Directions

Pump enough product in your palm to thoroughly cover your hands. Rub hands together briskly until dry. Children under 6 years of age should be supervised when using this product.

Inactive Ingredients

Water, Polysorbate 20, Ethylhexyl Methoxycinnamate, Ethylhexyl Sallicylate, PPG-26-Buteth-26, PEG-40 Hydrogenated Castor Oil, Aloe Barbadensis Leaf Juice, Fragrance, Tetrasodium EDTA, DMDM Hydantoin, Sodium Hydroxide, Blue 1, Yellow 5

Package Front and Back Labels

ht.jpg